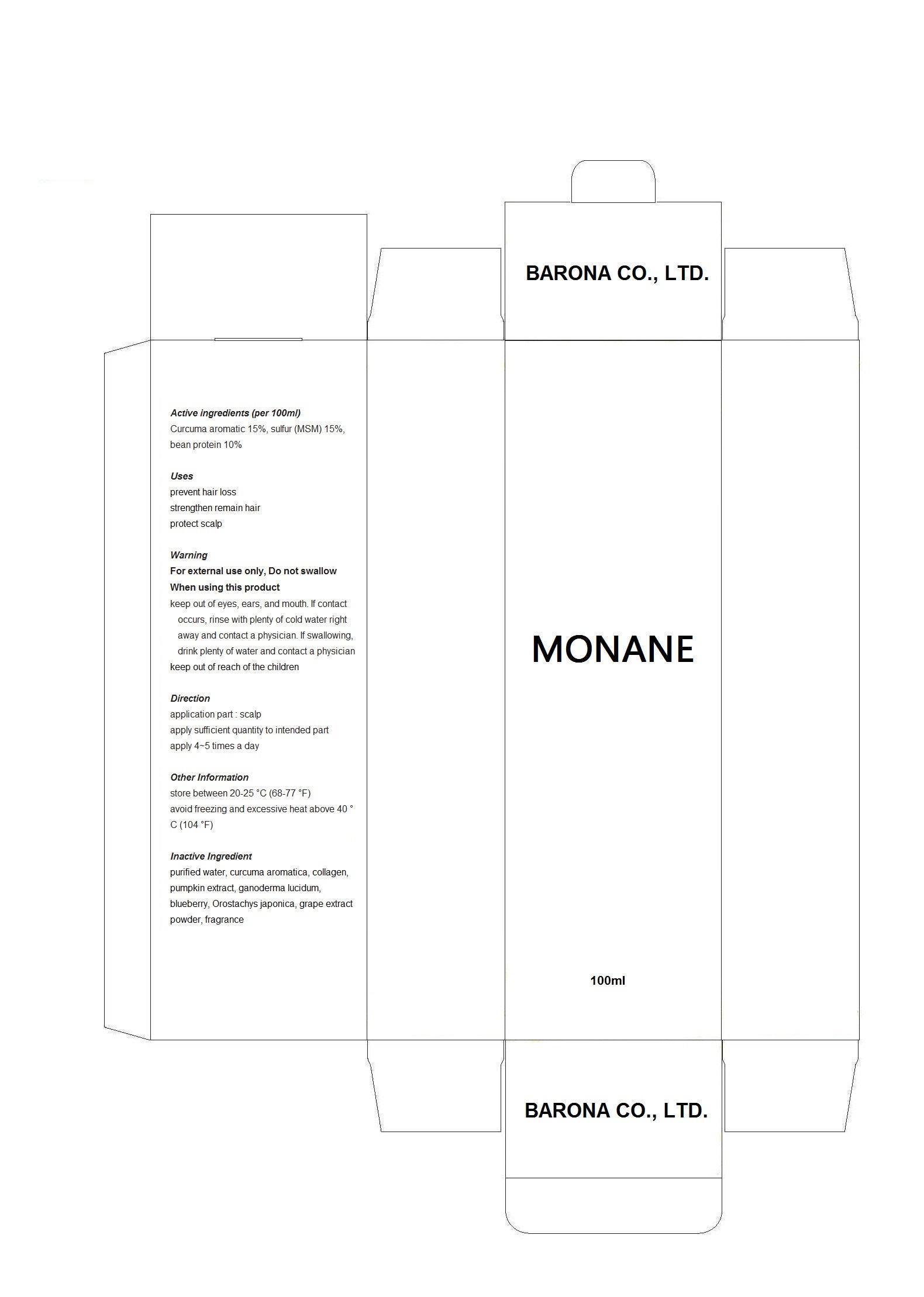 DRUG LABEL: MONANE
NDC: 61164-5001 | Form: LIQUID
Manufacturer: Barona Co., Ltd 
Category: otc | Type: HUMAN OTC DRUG LABEL
Date: 20150204

ACTIVE INGREDIENTS: CURCUMA AROMATICA ROOT OIL 15 g/100 mL
INACTIVE INGREDIENTS: WATER; ECLIPTA PROSTRATA LEAF

Drug Facts

ACTIVE INGREDIENT

CURCUMA AROMATICA ROOT OIL

INACTIVE INGREDIENT

sulfur (MSM), bean protein, purified water, curcuma aromatica, collagen, pumpkin extract, ganoderma lucidum, blueberry, Orostachys japonica, grape extract powder, fragrance

PURPOSE

prevent hair loss
strengthen remain hair
protect scalp

keep out or reach of the children

INDICATIONS AND USAGE

apply 4% times everyday to the scalp and rub softly

WARNINGS

do not swallow

DOSAGE AND ADMINISTRATION

for topical use only